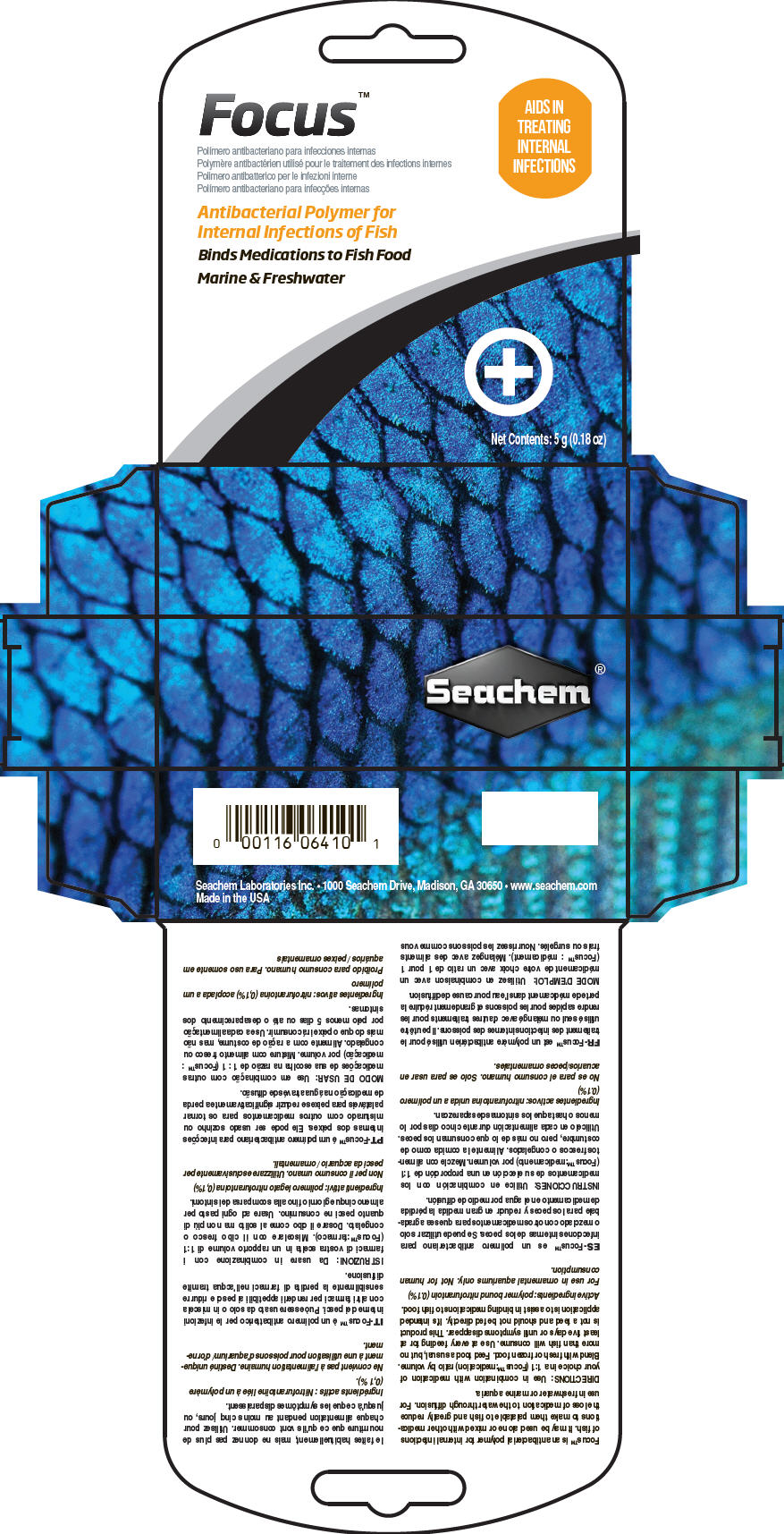 DRUG LABEL: Focus
NDC: 55999-065 | Form: POWDER
Manufacturer: Seachem Laboratories Inc.
Category: animal | Type: OTC ANIMAL DRUG LABEL
Date: 20190807

ACTIVE INGREDIENTS: Nitrofurantoin 1 mg/1 g

Focus™

VETERINARY INDICATIONS

Focus™ is an antibacterial polymer for internal infections of fish. It may be used alone or mixed with other medications to make them palatable to fish and greatly reduce the loss of medication to the water through diffusion. For use in freshwater or marine aquaria.

DOSAGE AND ADMINISTRATION

DIRECTIONS: Use in combination with medication of your choice in a 1:1 (Focus™:medication) ratio by volume. Blend with fresh or frozen food. Feed food as usual, but no more than fish will consume. Use at every feeding for at least five days or until symptoms disappear. This product is not a feed and should not be fed directly. It's intended application is to assist in binding medications to fish food.

Active ingredients: polymer bound nitrofurantoin (0.1%)

SAFE HANDLING WARNING

For use in ornamental aquariums only. Not for human consumption.

PRINCIPAL DISPLAY PANEL - 5 g Vial Carton

Focus™

AIDS IN
TREATING
INTERNAL
INFECTIONS

Antibacterial Polymer for
Internal Infections of Fish

Binds Medications to Fish Food

Marine & Freshwater

Net Contents: 5 g (0.18 oz)